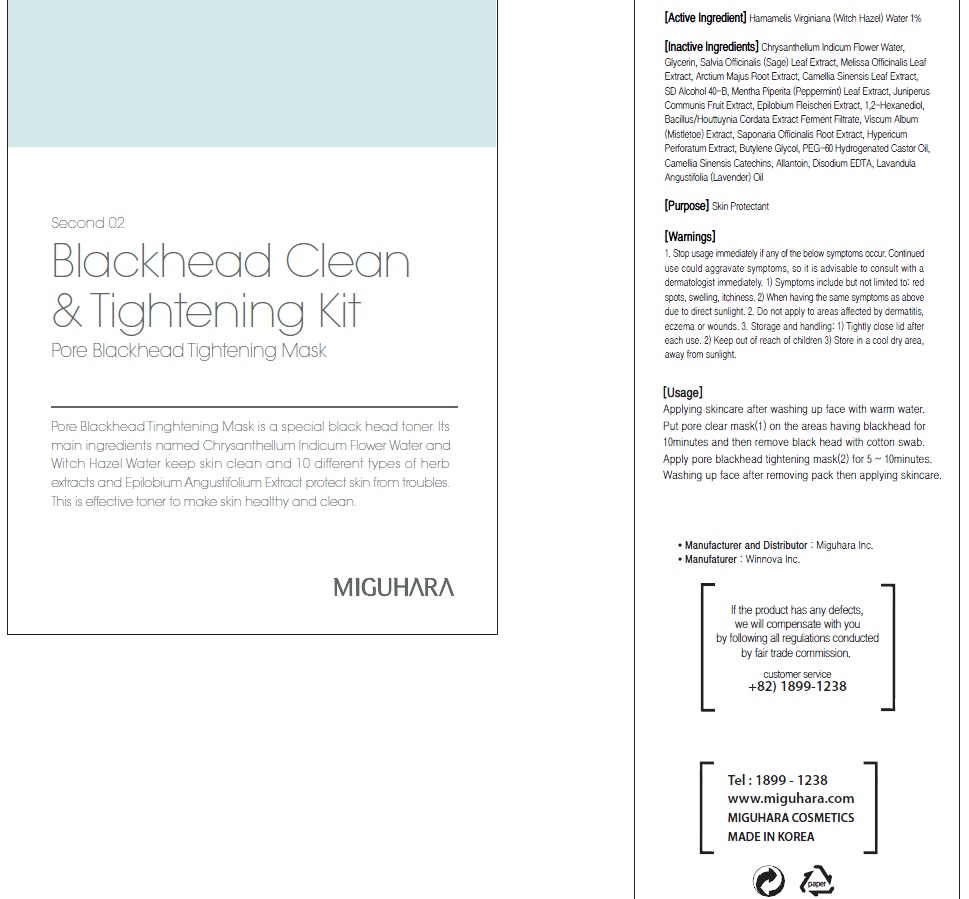 DRUG LABEL: Pore Blackhead Tightening Mask
NDC: 70380-290 | Form: PATCH
Manufacturer: MIGUHARA
Category: otc | Type: HUMAN OTC DRUG LABEL
Date: 20160224

ACTIVE INGREDIENTS: Witch Hazel 0.03 g/10 1
INACTIVE INGREDIENTS: CHRYSANTHELLUM INDICUM FLOWER OIL; Glycerin

ACTIVE INGREDIENT

Active Ingredient: Hamamelis Virginiana (Witch Hazel) Water 1%

INACTIVE INGREDIENT

Inactive Ingredients: Chrysanthellum Indicum Flower Water, Glycerin, Salvia Officinalis (Sage) Leaf Extract, Melissa Officinalis Leaf Extract, Arctium Majus Root Extract, Camellia Sinensis Leaf Extract, SD Alcohol 40-B, Mentha Piperita (Peppermint) Leaf Extract, Juniperus Communis Fruit Extract, Epilobium Fleischeri Extract, 1,2-Hexanediol, Bacillus/Houttuynia Cordata Extract Ferment Filtrate, Viscum Album (Mistletoe) Extract, Saponaria Officinalis Root Extract, Hypericum Perforatum Extract, Butylene Glycol, PEG-60 Hydrogenated Castor Oil, Camellia Sinensis Catechins, Allantoin, Disodium EDTA, Lavandula Angustifolia (Lavender) Oil

PURPOSE

Purpose: Skin Protectant

WARNINGS

1. Stop usage immediately if any of the below symptoms occur. Continued use could aggravate symptoms, so it is advisable to consult with a dermatologist immediately. 1) Symptoms include but not limited to: red spots, swelling, itchiness. 2) When having the same symptoms as above due to direct sunlight. 2. Do not apply to areas affected by dermatitis, eczema or wounds. 3. Storage and handling: 1) Tightly close lid after each use. 2 Keep out of reach of children 3) Store in a cool dry area, away from sunlight

KEEP OUT OF REACH OF CHILDREN

Usage

Usage: Applying skincare after washing up face with warm water. Put pore clear mask(1) on the areas having blackhead for 10minutes and then remove black head with cotton swab. Apply pore blackhead tightening mask(2) for 5 ~ 10minutes. Washing up face after removing pack then applying skincare.

Usage

Usage: Applying skincare after washing up face with warm water. Put pore clear mask(1) on the areas having blackhead for 10minutes and then remove black head with cotton swab. Apply pore blackhead tightening mask(2) for 5 ~ 10minutes. Washing up face after removing pack then applying skincare.